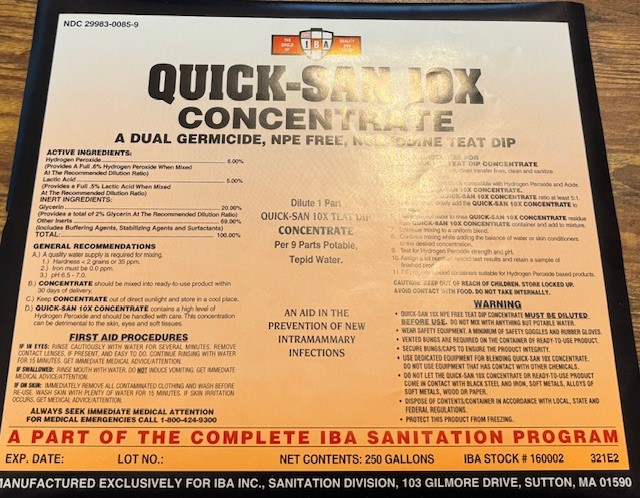 DRUG LABEL: Quick-San 10X Concentrate
NDC: 29983-0085 | Form: SOLUTION
Manufacturer: IBA
Category: animal | Type: OTC ANIMAL DRUG LABEL
Date: 20241226

ACTIVE INGREDIENTS: HYDROGEN PEROXIDE 60.0 g/1 L; LACTIC ACID 50.0 g/1 L

QUICK-SAN 10X CONCENTRATE A DUEL GERMICIDE, NPE FREE, NON-IODINE TEAT DIP

ACTIVE INGREDIENT

Hydrogen Peroxide...........6.00%

(Provides a A Full .60% Hydrogen Peroxide When Mixed At teh Recommended Dilution Ratio)

Lactic Acid.....................0.50%

(Provides a A Full .50% Lactic Acid When Mixed At teh Recommended Dilution Ratio)
INERT INGREDIENTS
Emollients(skin conditioners)...........20.00%

(Provides a A Total.2.00% Glycerin When Mixed At teh Recommended Dilution Ratio)
Other Inerts.....69.00%
(Includes Buffering Agents, Wetting Agents, Stabilizing Agents, and Colorants)
Total.................100%

Diluet 1 Part QUICK-SAN 10X TEAT DIP CONCENTRATE Per 9 Parts Potable, Tepid Water

An AID IN THE PREVENTION OF NEW INTRAMAMMARY INFECTIONS

INDICATIONS AND USAGE

GENERAL RECOMMENDATIONS

A.) A Qaulity water supply is required for mixing

1. Hardness <2 grains or 35 ppm

2. Iron must be 0.0 ppm

3. pH 6.5-7.0

B.) CONCENTRATE should be mixed ready-to-use product within 30 days of delivery

C.) Keep CONCENTRATE out of direct sunlight and store in a cool place

D.) QUICK-SAN 10X CONCENTRATE contains a high level of Hydrogen Peroxide and should be handled with care. This concentration can be detrimental to the skin, eyes and soft tissues.

MIXING GUILDINES FOR QUICK-SAN 10xX TEAT DIP CONCENTRATE

1. Clean mixing equipment, clean transfer lines, clean and sanitize packing containers.
2. Use only equipment that is compatible with Hydrogen Peroxide and Acids.
3. Start with QUICK- SAN 10X CONCENTRATE.
4. Water volume to QUICK- SAN 10X CONCENTRATE ratio at least 5:1.
5. With agitation, slowly add the QUICK- SAN 10X CONCENTRATE to the water.
6. Use additional water to rinse QUICK- SAN 10X CONCENTRATE residue from QUICK- SAN 10X CONCENTRATE container and add to mixture.
7. Continue mixing to a uniform blend.
8. Continue mixing while adding the balance of water or skin conditioners to the desired concentration.
9. Test for Hydrogen Peroxide strength pH.
10. Assign a lot number , record test results and retain a sample of finished product.
11. Fill properly labeled containers suitable for Hydrogen Peroxide based products.

CAUTION: KEEP OUT OF REACH OF CHILDREN, STORE LOCKED UP.
AVOID CONTACT WITH FOOD. DO NOT TAKE INTERNALLY.

WARNING

QUICK-SAN 10X NPE FREE TEAT DIP CONCENTRATE MUST BE DILUTED BEFORE USE. DO NOT MIX WITH ANYTHING BUT POTABLE WATER.
WEAR SAFETY EQUIPMENT. A MINIMUM OF SAFETY GOGGLES AND RUBBER GLOVES.
VENTED BUNGS ARE REQUIRED ON THE CONTAINER OF READY-TO-USE PRODUCT.
SECURE BUNGS/CAPS TO ENSURE THE PRODUCT INTEGRITY.
USE DEDICATED EQUIPMENT FOR BLENDING QUICK-SAN 10X CONCENTRATE. DO NOT USE EQUIPMENT THAT HAS CONTACT WITH OTHER CHEMICALS.
DO NOT LET THE QUICK-SAN 10X CONCENTRATE OR READY-TO-USE PRODUCT COME INTO CONTACT WITH BLACK STEEL AND IRON, SOFT METALS, ALLOYS OF SOFT METALS, WOODOR PAPER.
DISPOSE OF CONTENTS/CONTAINER IN ACCORDANCE WITH LOCAL, STATE AND FEDERAL REGULATIONS.
PROTECT THIS PRODUCT FROM FREEZING
Close

FIRST AID PROCEDURES

IF IN EYES: RINSE CAUTIOUSLY WITH WATER FOR SEVERAL MINUTES. REMOVE CONTACT LENSES, IF PRESENT, AND EASY TO DO. CONTINUE RINSING WITH WATAER FOR 15 MINUTES. GET IMMEDIATE MEDICAL ADVICE/ATTENTION.

IF SWALLOWED: RINSE MOUTH WITH WATER. DO NOTH INDUCE VOMITING. GET IMMEDIATE MEDICAL ADVICE/ATTENTION.

IF ON SKIN: IMMEDIATELY REMOVE ALL CONTAMINATED CLOTHING AND WASH BEFORE RE-USE. WASH SKIN WITH PLENTY OF WATER FOR 15 MINUTES. IF SKIN IRRITATION OCCURS, GET MEDICAL ADVICE/ATTENTION

ALWAYS SEEK IMMEDIATE MEDICAL ATTENTION
FOR MEDICAL EMERGENCIES CALL 1-800-424-9300